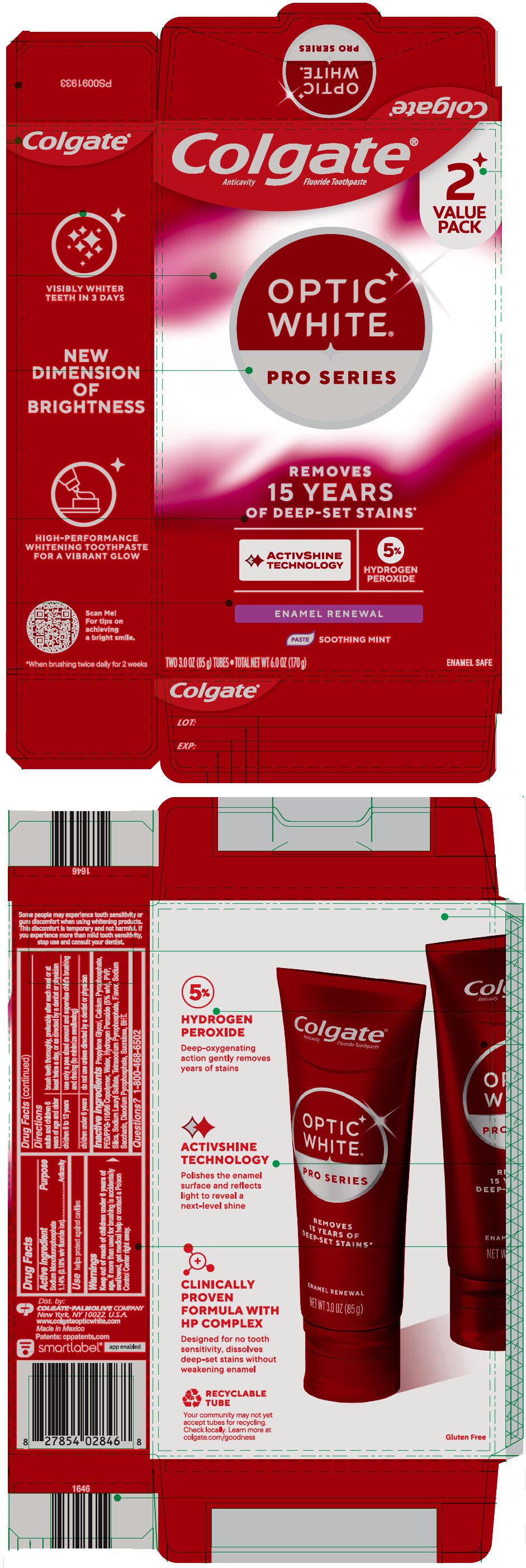 DRUG LABEL: COLGATE OPTIC WHITE PRO SERIES
NDC: 65954-845 | Form: PASTE, DENTIFRICE
Manufacturer: Mission Hills, S.A. de C.V.
Category: otc | Type: HUMAN OTC DRUG LABEL
Date: 20251223

ACTIVE INGREDIENTS: SODIUM MONOFLUOROPHOSPHATE 11.4 mg/1 g
INACTIVE INGREDIENTS: PROPYLENE GLYCOL 560.3 mg/1 g; CALCIUM PYROPHOSPHATE; PEG/PPG-116/66 COPOLYMER; WATER; HYDROGEN PEROXIDE; POVIDONE K30; HYDRATED SILICA; SODIUM LAURYL SULFATE; SODIUM PYROPHOSPHATE; SACCHARIN SODIUM; SODIUM ACID PYROPHOSPHATE; SUCRALOSE; BUTYLATED HYDROXYTOLUENE

COLGATE® OPTIC WHITE® PRO SERIES

Drug Facts

Active ingredient

Sodium Monofluorophosphate 1.14% (0.18% w/v fluoride ion)

Purpose

Anticavity

Use

helps protect against cavities

Warnings

Keep out of reach of children under 6 years of age. If more than used for brushing is accidentally swallowed, get medical help or contact a Poison Contol Center right away.

Directions

adults and children 6 years of age and older | brush teeth thoroughly, preferably after each meal or at least twice a day, or as directed by a dentist or physician
children 6 to 12 years | use only a pea sized amount and supervise child's brushing and rinsing (to minimize swallowing)
children under 6 years | do not use unless directed by a dentist or physician

Inactive ingredients

Propylene Glycol, Calcium Pyrophosphate, PEG/PPG-116/66 Copolymer, Water, Hydrogen Peroxide (5% w/v), PVP, Silica, Sodium Lauryl Sulfate, Tetrasodium Pyrophosphate, Flavor, Sodium Saccharin, Disodium Pyrophosphate, Sucralose, BHT.

Questions?

1-800-468-6502

Dist. by:
COLGATE-PALMOLIVE COMPANY
New York, NY 10022, U.S.A.

PRINCIPAL DISPLAY PANEL - 85 g Tube Carton

Colgate®
Anticavity Fluoride Toothpaste

2
VALUE
PACK

OPTIC
WHITE®

PRO SERIES

REMOVES
15 YEARS
OF DEEP-SET STAINS*

ACTIVSHINE
TECHNOLOGY

5%
HYDROGEN
PEROXIDE

ENAMEL RENEWAL

PASTE
SOOTHING MINT

TWO 3.0 OZ (85 g) TUBES • TOTAL NET WT 6.0 OZ (170 g)
ENAMEL SAFE